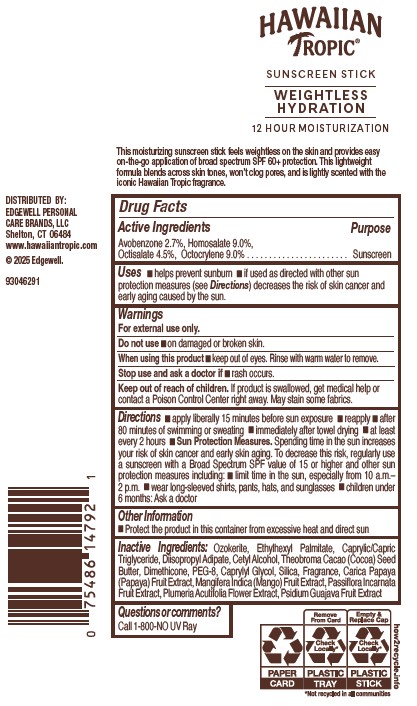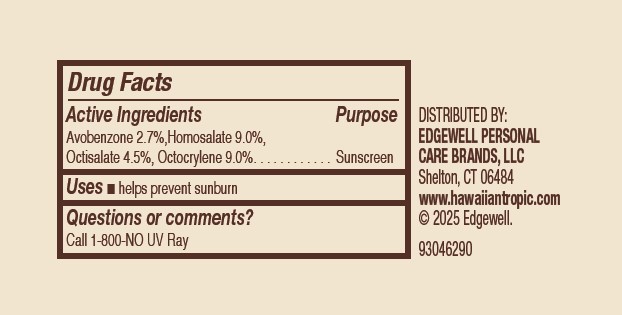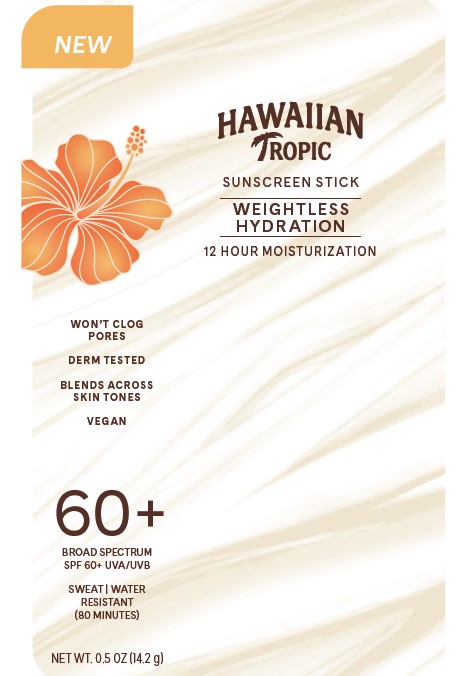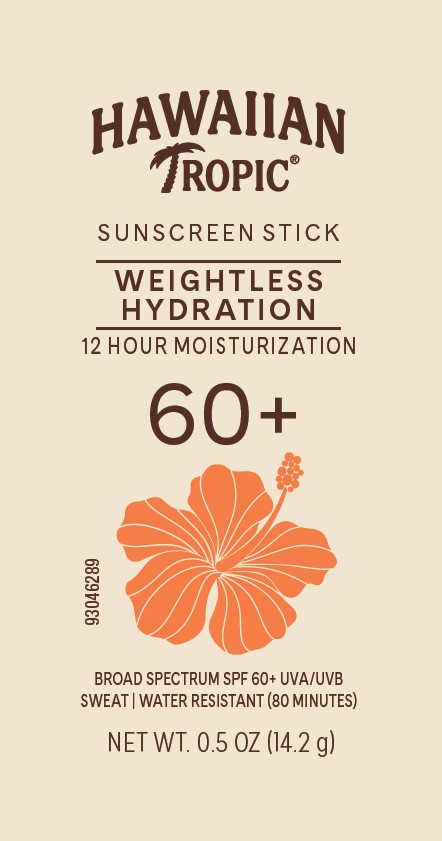 DRUG LABEL: HAWAIIAN TROPIC
NDC: 63354-861 | Form: STICK
Manufacturer: Edgewell Personal Care Brands LLC
Category: otc | Type: HUMAN OTC DRUG LABEL
Date: 20250312

ACTIVE INGREDIENTS: OCTISALATE 4.5 g/100 g; HOMOSALATE 9 g/100 g; AVOBENZONE 2.7 g/100 g; OCTOCRYLENE 9 g/100 g
INACTIVE INGREDIENTS: CAPRYLYL GLYCOL; PSIDIUM GUAJAVA FRUIT; ETHYLHEXYL PALMITATE; CETYL ALCOHOL; THEOBROMA CACAO (COCOA) SEED BUTTER; CARICA PAPAYA (PAPAYA) FRUIT; DIMETHICONE; SILICA; MANGIFERA INDICA (MANGO) FRUIT; DIISOPROPYL ADIPATE; PEG-8; PASSIFLORA INCARNATA FRUIT; CERESIN; PLUMERIA RUBRA FLOWER; CAPRYLIC/CAPRIC TRIGLYCERIDE

Active Ingredients

Avobenzone 2.7%, Homosalate 9.0%, Octisalate 4.5%, Octocrylene 9.0%

Purpose

Sunscreen

Uses

■ helps prevent sunburn ■ if used as directed with other sun protection measures (see Directions) decreases the risk of skin cancer and early aging caused by the sun

Warnings

For external use only.

May stain some fabrics.

Do not use

■ on damaged or broken skin.

When using this product

■ keep out of eyes. Rinse with warm water to remove.

Stop use and ask a doctor if

■ rash occurs.

Keep out of reach of children.

If product is swallowed, get medical help or contact a Poison Control Center right away.

Directions

■ apply liberally 15 minutes before sun exposure ■ reapply ■ after 80 minutes of swimming or sweating ■ immediately after towel drying ■ at least every 2 hours ■ Sun Protection Measures. Spending time in the sun increases your risk of skin cancer and early skin aging. To decrease this risk, regularly use a sunscreen with a Broad Spectrum SPF value of 15 or higher and other sun protection measures including: ■ limit time in the sun, especially from 10 a.m.–2 p.m. ■ wear long-sleeved shirts, pants, hats, and sunglasses ■ children under 6 months: Ask a doctor

Other Information

■ Protect the product in this container from excessive heat and direct sun

Inactive Ingredients:

Ozokerite, Ethylhexyl Palmitate, Caprylic/Capric Triglyceride, Diisopropyl Adipate, Cetyl Alcohol, Theobroma Cacao (Cocoa) Seed Butter, Dimethicone, PEG‐8, Caprylyl Glycol, Silica, Fragrance, Carica Papaya (Papaya) Fruit Extract, Mangifera Indica (Mango) Fruit Extract, Passiflora Incarnata Fruit Extract, Plumeria Acutifolia Flower Extract, Psidium Guajava Fruit Extract

Questions or comments?

Call 1-800-NO UV Ray

Principal Display Panel

HAWAIIAN TROPIC

SUNSCREEN STICK

WEIGHTLESS

HYDRATION

12 HOUR MOISTURIZATION

60+

BROAD SPECTRUM SPF 60+ UVA/UVB

SWEAT | WATER RESISTANT (80 MINUTES)

NET WT. 0.5 OZ (14.2 g)

NEW

HAWAIIAN

TROPIC

SUNSCREEN STICK

WEIGHTLESS

HYDRATION

12 HOUR MOISTURIZATION

WON'T CLOG

PORES

DERM TESTED

BLENDS ACROSS

SKIN TONES

VEGAN

60+

BROAD SPECTRUM

SPF 60+ UVA/UVB

SWEAT | WATER

RESISTANT

(80 MINUTES)

NET WT. 0.5 OZ (14.2 g)